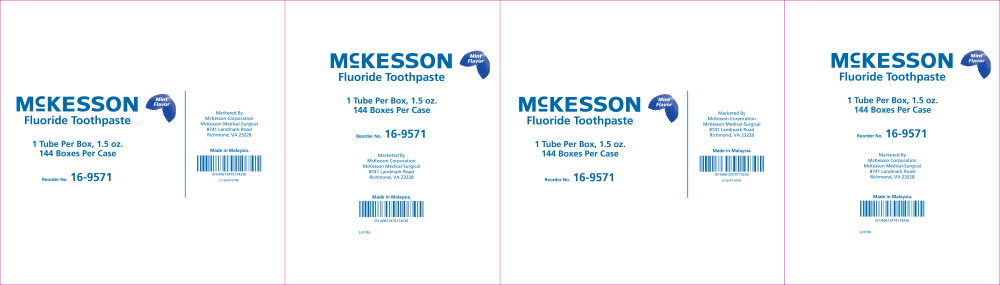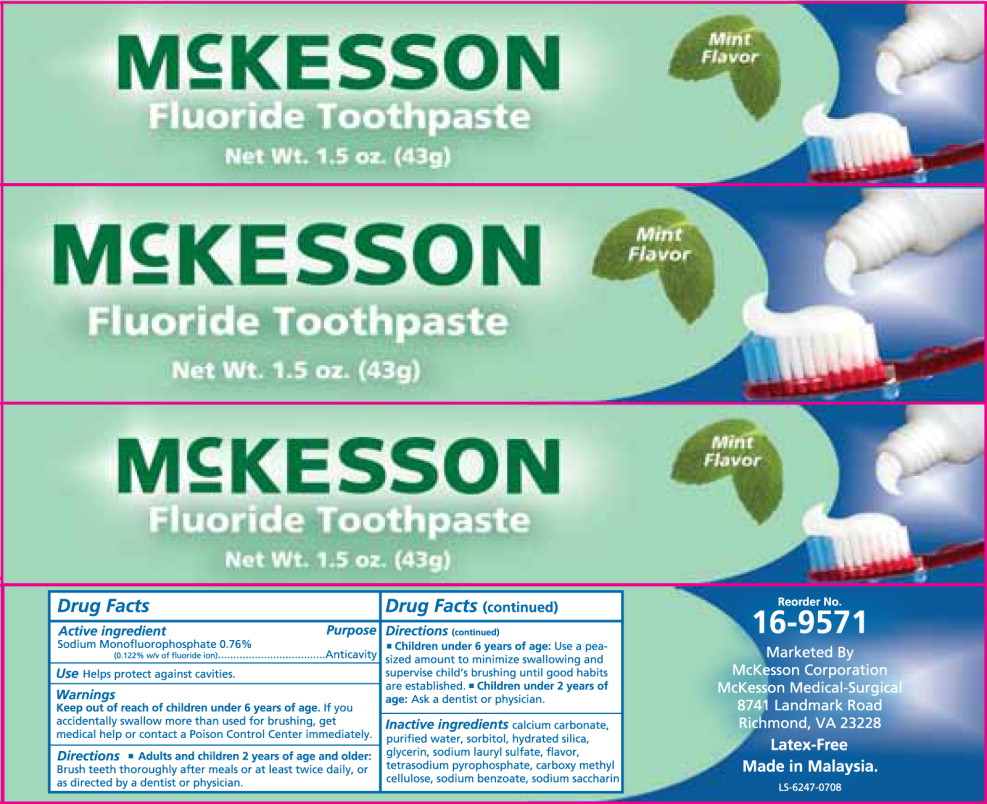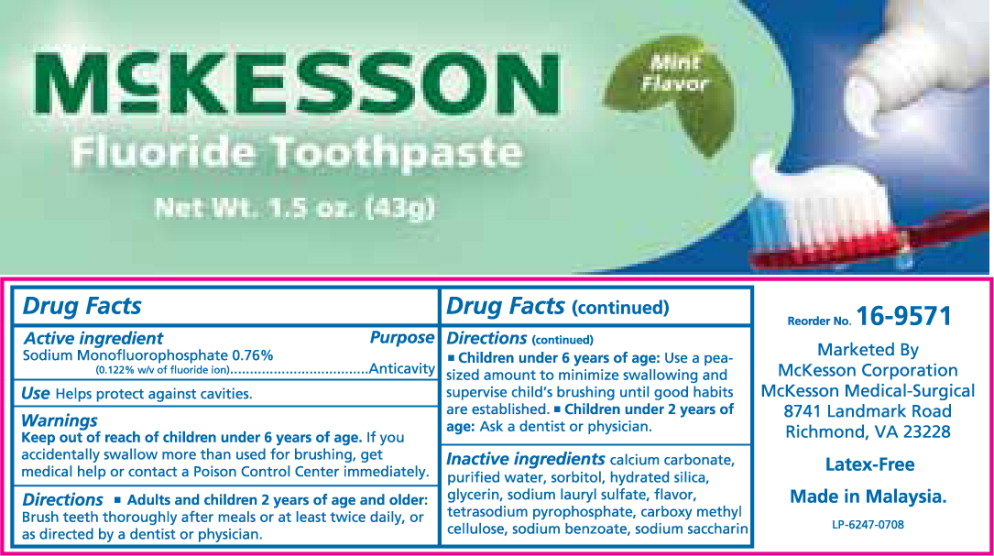 DRUG LABEL: McKesson Fluoride
NDC: 68599-0123 | Form: PASTE, DENTIFRICE
Manufacturer: McKesson Medical-Surgical
Category: otc | Type: HUMAN OTC DRUG LABEL
Date: 20241010

ACTIVE INGREDIENTS: SODIUM MONOFLUOROPHOSPHATE 2.43 mg/1 g
INACTIVE INGREDIENTS: CALCIUM CARBONATE; WATER; SORBITOL; HYDRATED SILICA; GLYCERIN; SODIUM LAURYL SULFATE; SODIUM PYROPHOSPHATE; CARBOXYMETHYLCELLULOSE; SODIUM BENZOATE; SACCHARIN SODIUM

68599-0123

Drug Facts

Active Ingredient

Sodium Monofluorophosphate 0.76% (0.122% w/v of fluoride ion)

Purpose

Anticavity

Use

Helps protect against cavities.

Keep out of reach of children under 6 years of age.If you accidentally swallow more than used for brushing, get medical help or contact a Poison Control Center immediately.

Directions

- Adults and children 2 years of age and older:Brush teeth thoroughly after meals or at least twice daily, or as directed by a dentist or physician.
- Children under 6 years of age:Use a pea-sized amount to minimize swallowing and supervise child's brushing until good habits are established.
- Children under 2 years of age:Ask a dentist or physician.

Inactive ingredients

calcium carbonate, purified water, sorbitol, hydrated silica, glycerin, sodium lauryl sulfate, flavor, tetrasodium pyrophosphate, carboxy methyl cellulose, sodium benzoate, sodium saccharin

Principal Display Panel – 1.5 oz Case Label

Mint
Flavor

Mc KESSON
Fluoride Toothpaste

1 Tube per Box, 1.5 oz
144 Boxes Per Case

Reorder No. 16-9571

Principal Display Panel – 1.5 oz Box Label

Mint
Flavor

Mc KESSON
Fluoride Toothpaste

Net Wt. 1.5 oz. (43g)

Principal Display Panel – 1.5 oz Tube Label

Mint
Flavor

Mc KESSON
Fluoride Toothpaste

Net Wt. 1.5 oz. (43g)